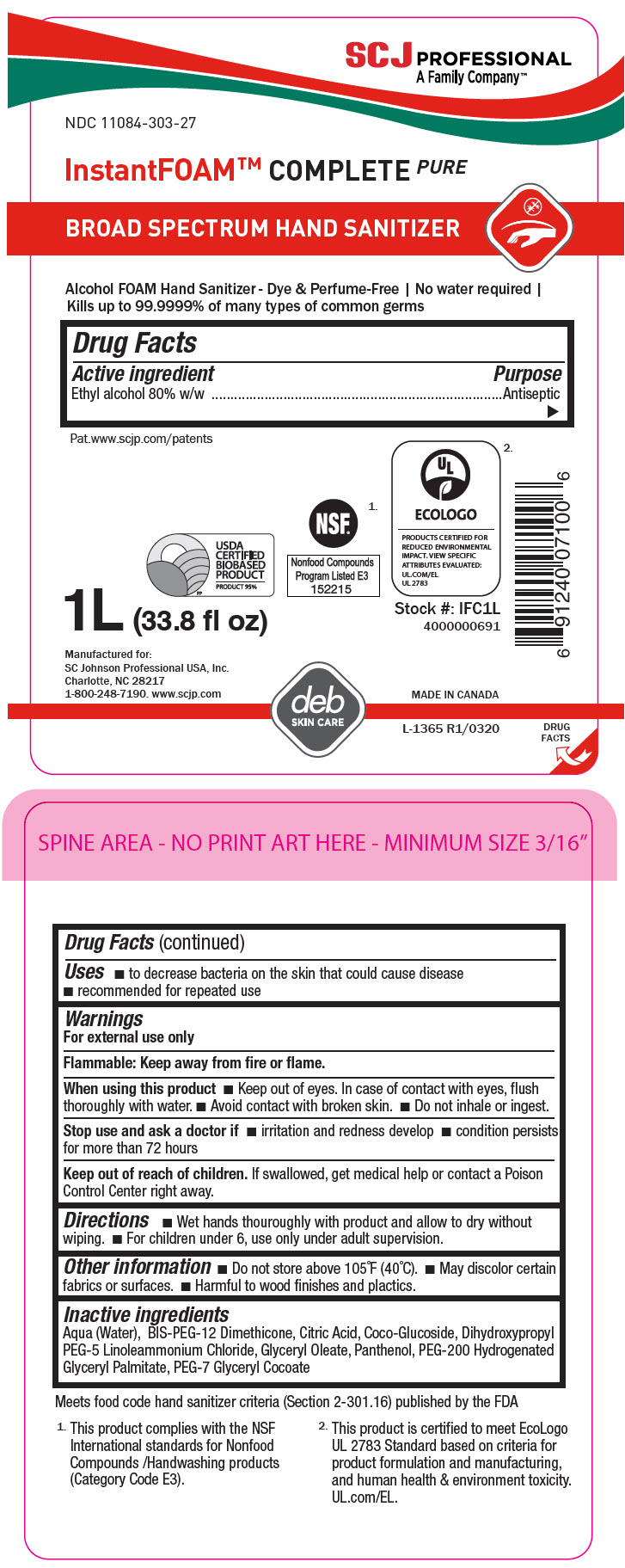 DRUG LABEL: InstantFoam Complete PURE
NDC: 11084-303 | Form: LIQUID
Manufacturer: SC Johnson Professional USA Inc.
Category: otc | Type: HUMAN OTC DRUG LABEL
Date: 20250620

ACTIVE INGREDIENTS: ALCOHOL 80 g/100 mL
INACTIVE INGREDIENTS: WATER; ANHYDROUS CITRIC ACID; BIS-PEG-12 DIMETHICONE (500 MPA.S); COCO-GLUCOSIDE; PEG-7 GLYCERYL COCOATE; GLYCERYL OLEATE; PANTHENOL; PEG-200 HYDROGENATED GLYCERYL PALMATE; DIHYDROXYPROPYL PEG-5 LINOLEAMMONIUM CHLORIDE

InstantFoam™ Complete PURE

Drug Facts

Active ingredient

Ethyl alcohol 80% w/w

Purpose

Antiseptic

Uses

- to decrease bacteria on the skin that could cause disease
- recommended for repeated use

Warnings

For external use only

Flammable: Keep away from fire or flame.

When using this product

- Keep out of eyes. In case of contact with eyes, flush thoroughly with water.
- Avoid contact with broken skin.
- Do not inhale or ingest.

Stop use and ask a doctor if

- irritation and redness develop
- condition persists for more than 72 hours

Keep out of reach of children. If swallowed, get medical help or contact a Poison Control Center right away.

Directions

- Wet hands thouroughly with product and allow to dry without wiping.
- For children under 6, use only under adult supervision.

Other information

- Do not store above 105°F (40°C).
- May discolor certain fabrics or surfaces.
- Harmful to wood finishes and plactics.

Inactive ingredients

Aqua (Water), BIS-PEG-12 Dimethicone, Citric Acid, Coco-Glucoside, Dihydroxypropyl PEG-5 Linoleammonium Chloride, Glyceryl Oleate, Panthenol, PEG-200 Hydrogenated Glyceryl Palmitate, PEG-7 Glyceryl Cocoate

PRINCIPAL DISPLAY PANEL - 1 L Bottle Label

SCJ PROFESSIONAL
A Family Company™

NDC 11084-303-27

InstantFOAM™ COMPLETEPURE

BROAD SPECTRUM HAND SANITIZER

Alcohol FOAM Hand Sanitizer - Dye & Perfume-Free | No water required |
Kills up to 99.9999% of many types of common germs

Pat.www.scjp.com/patents

USDA
CERTIFIED
BIOBASED
PRODUCT
PRODUCT 95%

NSF®^1.
Nonfood Compounds
Program Listed E3
152215

UL ^2.
ECOLOGO
PRODUCTS CERTIFIED FOR
REDUCED ENVIRONMENTAL
IMPACT. VIEW SPECIFIC
ATTRIBUTES EVALUATED:
UL.COM/EL
UL 2783

1L (33.8 fl oz)

Stock #: IFC1L
4000000691

Manufactured for:
SC Johnson Professional USA, Inc.
Charlotte, NC 28217
1-800-248-7190. www.scjp.com

MADE IN CANADA

deb
SKIN CARE

L-1365 R1/0320

DRUG
FACTS